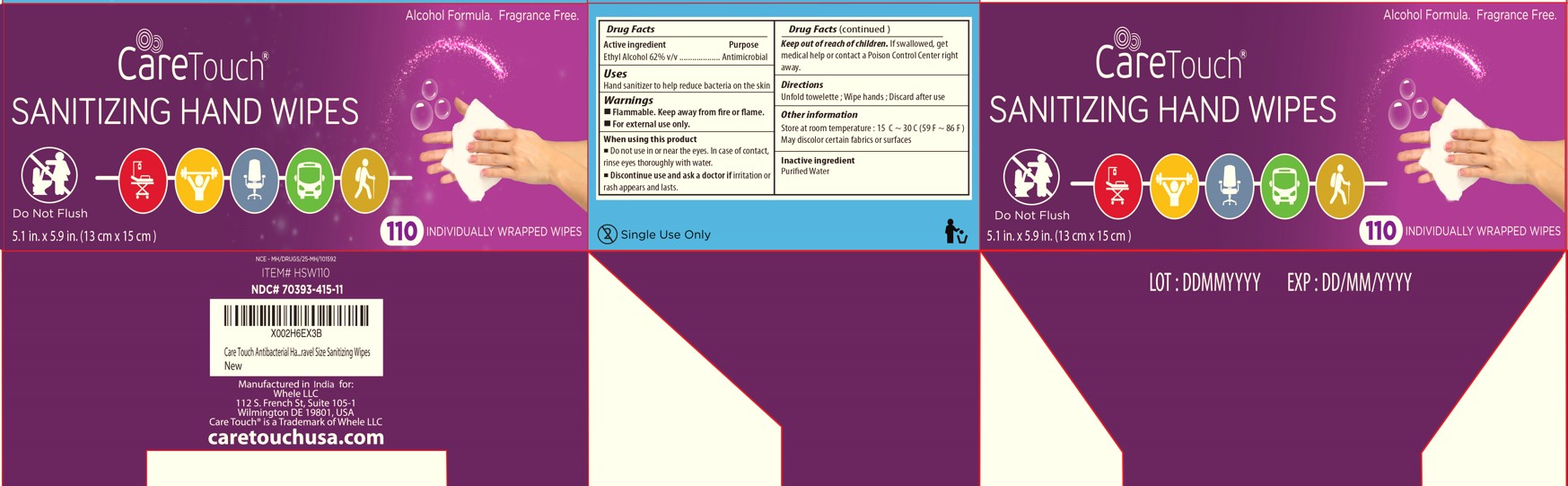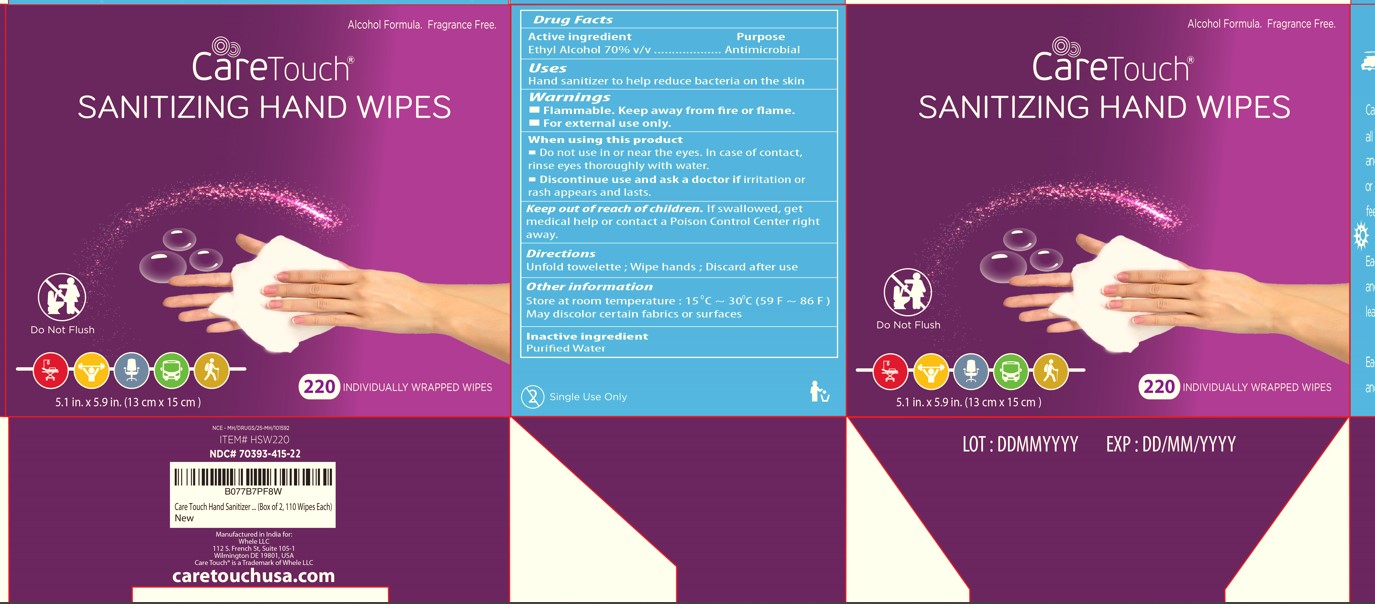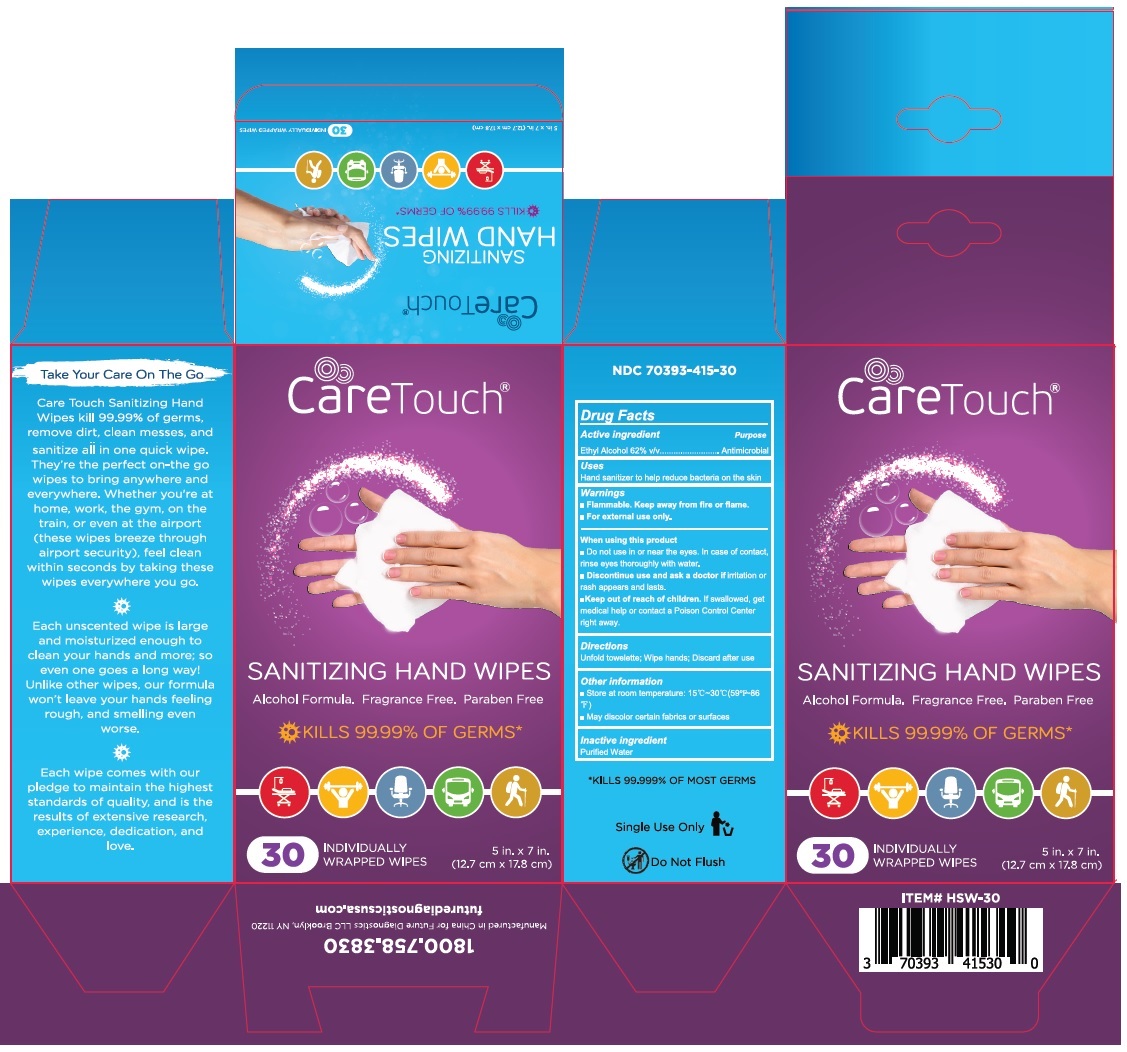 DRUG LABEL: CareTouch
NDC: 70393-415 | Form: CLOTH
Manufacturer: Future Diagnostics Llc
Category: otc | Type: HUMAN OTC DRUG LABEL
Date: 20251023

ACTIVE INGREDIENTS: ALCOHOL 0.62 mL/1 mL
INACTIVE INGREDIENTS: WATER

CareTouch Hand Sanitizer

Active ingredient

Ethyl Alcohol 62% v/v

Purpose

Antimicrobial

Uses

Hand sanitizer to help reduce bacteria on the skin

Warnings

■ Flammable. Keep away from fire or flame.
■ For external use only.

When using this product
■ Do not use in or near the eyes. In case of contact, rinse eyes thoroughly with water.
■ Discontinue use and ask a doctor if irritation or rash appears and lasts.

Keep out of reach of children. If swallowed, get medical help or contact a Poison Control Center right away.

Directions

Unfold towelette; Wipe hands; Discard after use

Inactive ingredient

Purified Water

Other information

■ Store at room temperature: 15℃~30℃(59℉~86℉)
■ May discolor certain fabrics or surfaces

Alcohol Formula. Fragrance Free. Paraben Free

INDIVIDUALLY WRAPPED WIPES

KILLS 99.99% OF GERMS

Take Your Care On the Go

Care Touch Sanitizing Hand Wipes kill 99.99% germs, remove dirt, clean messes, and sanitize all in one quick wipe. They're the perfect on-the go wipes to bring anywhere and everywhere. Whether you're at home, work, the gym, on the train, or even at the airport (these wipes breeze through airport security), feel clean within seconds by taking these wipes everywhere you go.

Each unscented wipe is large and moisturized enough to clean your hands and more; so even one goes a long way! Unlike other wipes, our formula won't leave your hands feeling rough, and smelling even worse.

Each wipe comes with our pledge to maintain the highest standards of quality, and is the results of extensive research, experience, dedication, and love.

1800.758.3830

Manufactured in China for Future Diagnostics LLC Brooklyn, NY 11220

futurediagnosticsusa.com